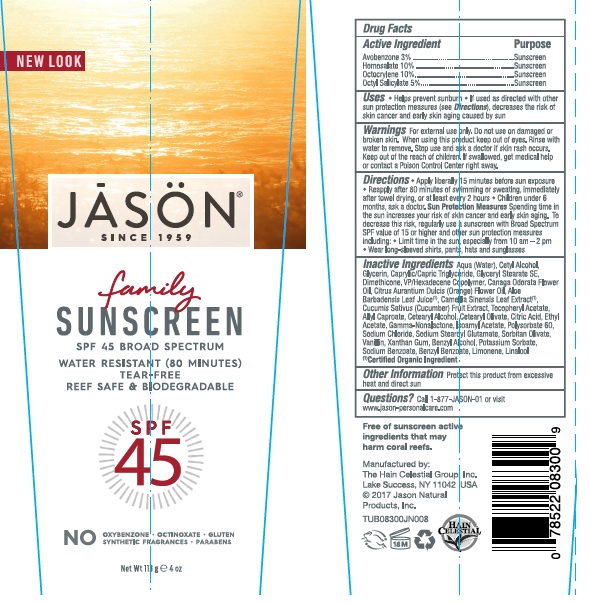 DRUG LABEL: J0830014 Jason Sun Family Sunscreen SPF45
NDC: 61995-0014 | Form: LOTION
Manufacturer: The Hain Celestial Group, Inc.
Category: otc | Type: HUMAN OTC DRUG LABEL
Date: 20210412

ACTIVE INGREDIENTS: HOMOSALATE 10 g/100 g; OCTISALATE 5 g/100 g; OCTOCRYLENE 10 g/100 g; AVOBENZONE 3 g/100 g
INACTIVE INGREDIENTS: VINYLPYRROLIDONE/HEXADECENE COPOLYMER; SODIUM STEAROYL GLUTAMATE; .ALPHA.-TOCOPHEROL ACETATE; GLYCERYL STEARATE SE; POTASSIUM SORBATE; CETYL ALCOHOL; DIMETHICONE; XANTHAN GUM; CETOSTEARYL ALCOHOL; POLYSORBATE 60; MEDIUM-CHAIN TRIGLYCERIDES; CETEARYL OLIVATE; SODIUM CHLORIDE; SORBITAN OLIVATE; SODIUM BENZOATE; BENZYL ALCOHOL; ALLYL HEXANOATE; CITRIC ACID MONOHYDRATE; GREEN TEA LEAF; CUCUMBER; ALOE VERA LEAF; GLYCERIN; WATER; CANANGA OIL; BENZYL BENZOATE; ORANGE OIL; ETHYL ACETATE; ISOAMYL ACETATE; VANILLIN; LIMONENE, (+)-; LINALOOL, (+/-)-

Jason Family Sunscreen SPF 45

Active Ingredient

Avobenzone - 3%

Homosalate - 10.0%

Octocrylene -10.0%

Octyl Salicylate - 5.0%

DOSAGE AND ADMINISTRATION

Apply liberally 15 minutes before sun exposure. Reapply after 80 minutes of swimming or sweating, immediately after towel drying and at least every 2 hours.

PURPOSE

Sunscreen

WARNINGS

For external use only. Do not use on damaged or broken skin. When using this product keep out of eyes. Rinse with water to remove. Stop use and ask a doctor if skin rash occurs.

Keep out of reach of children. If swallowed get medical help or contact Poison Center right away.

INACTIVE INGREDIENT

Water, Cetyl Alcohol, Glycerin, Caprylic/Capric Triglyceride, Glyceryl Stearate SE, Dimethicone, VP/Hexadecene Copolymer, Cananga Odorata Flower Oil, Citrus Aurantium Dulcis (Orange) Flower Oil, Aloe Barbadensis Leaf Juice(1), Camellia Sinensis Leaf Extract (1),Cucumis Sativus (Cucumber) Fruit Extract, Tocopheryl Acetate, Allyl Caproate, Cetearyl Alcohol, Cetearyl Olivate, Citric Acid, Ethyl Acetate, Gamma-Nonelactone, Isoamyl Acetate, Polysorbate 60, Sodium Chloride, Sodium Stearoyl Glutamate, Sorbitan Olivate, Vanillin, Xanthan Gum, Benzyl Alcohol, Potassium Sorbate, Sodium Benzoate, Benzyl Benzoate, Limonene, Linalool.

(1) Certified Organic Ingredient

INDICATIONS AND USAGE

Helps prevents sunburns. If used as directed with other sun protection measures, decreases risk of skin cancer and early skin aging caused by sun exposure. Skin Protection Measures: Spending time in the sun increases your risk of skin cancer and early skin aging. To decrease risk, regularly use sunscreen with Broad Spectrum SPF 15 or higher and other protective measures including: limit time in sun, especially from10am to 2pm, and wear long sleeved shirts, pants, hats and sunglases.